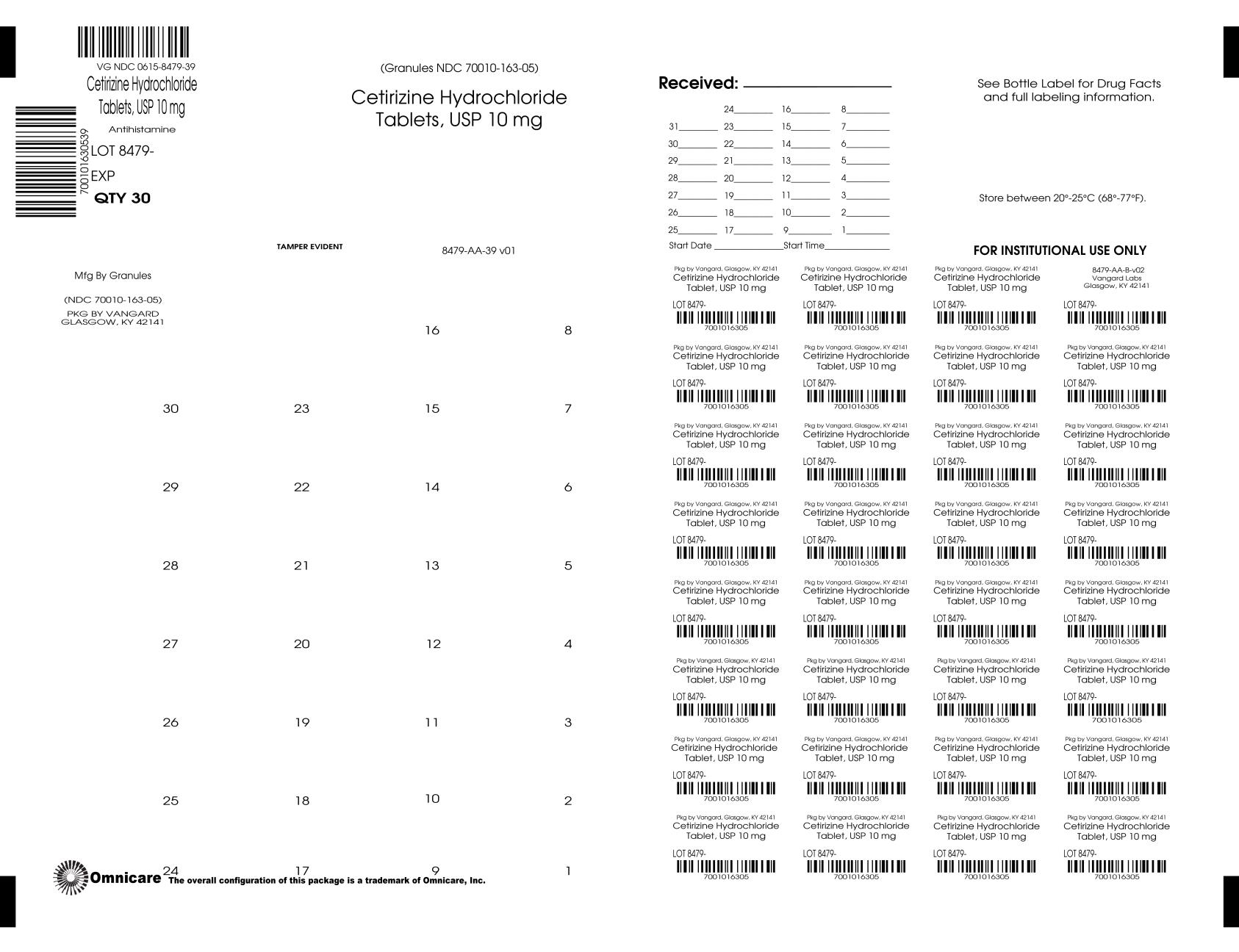 DRUG LABEL: Cetirizine hydrochloride
NDC: 0615-8479 | Form: TABLET, COATED
Manufacturer: NCS HealthCare of KY, LLC dba Vangard Labs
Category: otc | Type: HUMAN OTC DRUG LABEL
Date: 20240624

ACTIVE INGREDIENTS: CETIRIZINE HYDROCHLORIDE 10 mg/1 1
INACTIVE INGREDIENTS: LACTOSE MONOHYDRATE; CROSCARMELLOSE SODIUM; SILICON DIOXIDE; MAGNESIUM STEARATE; CELLULOSE, MICROCRYSTALLINE; HYPROMELLOSE, UNSPECIFIED; TITANIUM DIOXIDE; POLYETHYLENE GLYCOL, UNSPECIFIED

Cetrizine Hydrochloride Tablets

Cetirizine Hydrochloride Tablets

Drug Facts

Active Ingredient (in each tablet)

Cetirizine HCl 10 mg

PURPOSE

Antihistamine

USES

temporarily relieves these symptoms due to hay fever or other upper respiratory allergies:

- runny nose
- sneezing
- itchy, watery eyes
- itching of the nose or throat

WARNINGS

Do not use if you have ever had an allergic reaction to this product or any of its ingredients or to an antihistamine containing hydroxyzine.

ASK A DOCTOR BEFORE USE IF YOU HAVE

liver or kidney disease. Your doctor should determine if you need a different dose.

ASK A DOCTOR OR PHARMACIST BEFORE USE IF YOU ARE

taking tranquilizers or sedatives.

WHEN USING THIS PRODUCT

- drowsiness may occur
- avoid alcoholic drinks
- alcohol, sedatives, and tranquilizers may increase drowsiness
- be careful when driving a motor vehicle or operating machinery

STOP USE AND ASK DOCTOR IF

an allergic reaction to this product occurs. Seek medical help right away.

IF PREGNANT OR BREAST-FEEDING:

- if breast-feeding: not recommended
- if pregnant: ask a health professional before use.

KEEP OUT OF REACH OF CHILDREN

In case of overdose, get medical help or contact a Poison Control Center right away. (1-800-222-1222)

DIRECTIONS

adults and children 6 years and over | one 10 mg tablet once daily; do not take more than one 10 mg tablet in 24 hours. A 5 mg product may be appropriate for less severe symptoms.
adults 65 years and over | ask a doctor
children under 6 years of age | ask a doctor
consumers with liver or kidney disease | ask a doctor

OTHER INFORMATION

- store between 20° to 25°C (68° to 77°F)
- contains no ingredient made from a gluten-containing grain (Wheat, barley or rye).

Inactive ingredients

colloidal silicon dioxide, croscarmellose sodium, hypromellose, lactose monohydrate, magnesium stearate, microcrystalline cellulose, polyethylene glycol, titanium dioxide.

QUESTIONS?

call 1-877-770-3183: Mon-Fri 8:00 AM EST to 5:00 PM PST